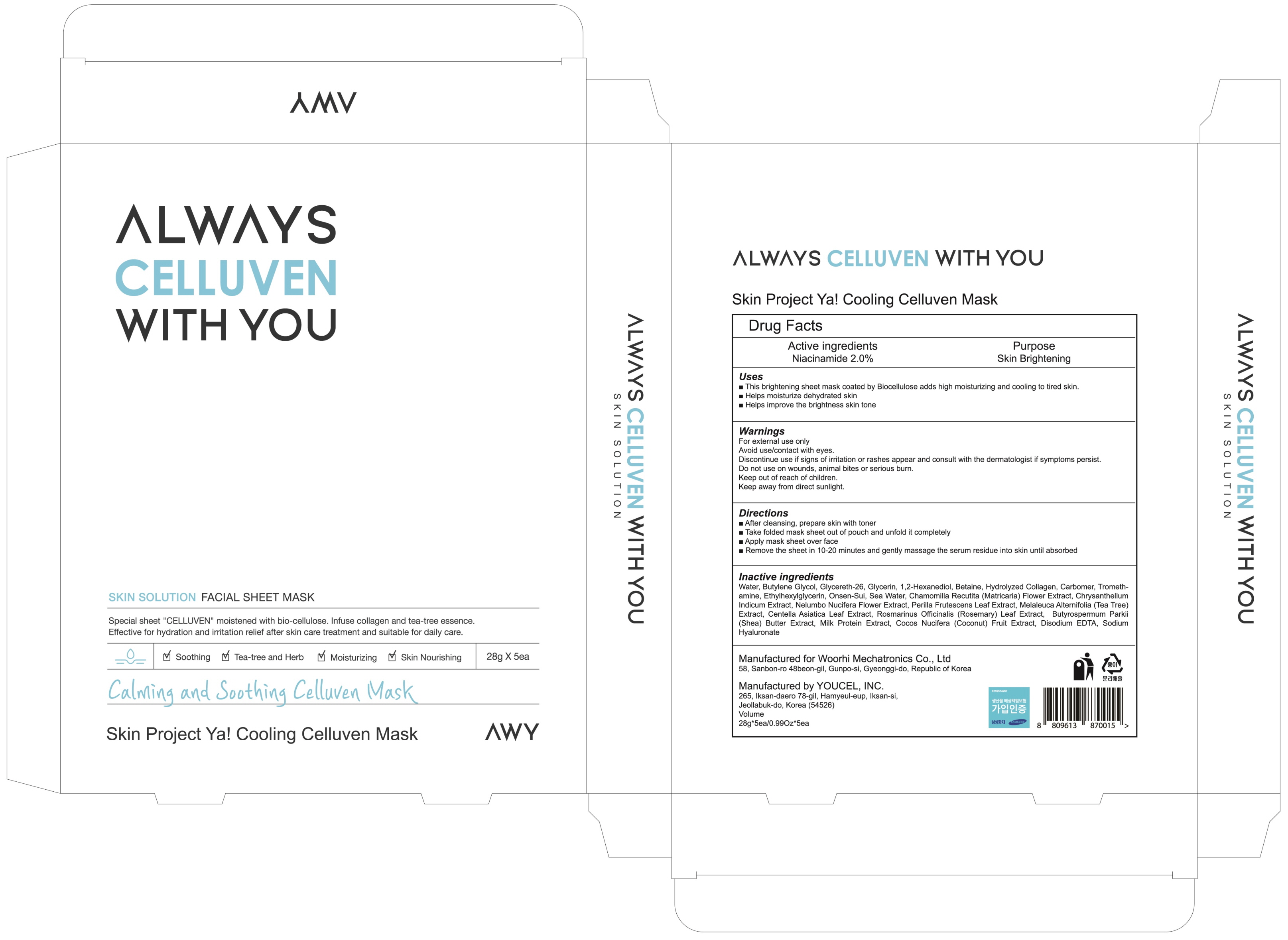 DRUG LABEL: Skin Project Ya Cooling Celluven Mask
NDC: 72729-040 | Form: PATCH
Manufacturer: Woorhi Mechatronics Co., Ltd.
Category: otc | Type: HUMAN OTC DRUG LABEL
Date: 20201218

ACTIVE INGREDIENTS: Niacinamide 0.56 g/28 g
INACTIVE INGREDIENTS: Water; Butylene Glycol

ACTIVE INGREDIENT

Niacinamide 2.0%

INACTIVE INGREDIENTS

Water, Butylene Glycol, Glycereth-26, Glycerin, 1,2-Hexanediol, Betaine, Hydrolyzed Collagen, Carbomer, Tromethamine, Ethylhexylglycerin, Onsen-Sui, Sea Water, Chamomilla Recutita (Matricaria) Flower Extract, Chrysanthellum Indicum Extract, Nelumbo Nucifera Flower Extract, Perilla Frutescens Leaf Extract, Melaleuca Alternifolia (Tea Tree) Extract, Centella Asiatica Leaf Extract, Rosmarinus Officinalis (Rosemary) Leaf Extract, Butyrospermum Parkii (Shea) Butter Extract, Milk Protein Extract, Cocos Nucifera (Coconut) Fruit Extract, Disodium EDTA, Sodium Hyaluronate

PURPOSE

Skin Brightening

WARNINGS

For external use only
Avoid use/contact with eyes.
Discontinue use if signs of irritation or rashes appear and consult with the dermatologist if symptoms persist.
Do not use on wounds, animal bites or serious burn.
Keep out of reach of children.
Keep away from direct sunlight.

KEEP OUT OF REACH OF CHILDREN

Uses

■ This brightening sheet mask coated by Biocellulose adds high moisturizing and cooling to tired skin.

■ Helps moisturize dehydrated skin

■ Helps improve the brightness skin tone

Directions

■ After cleansing, prepare skin with toner

■ Take folded mask sheet out of pouch and unfold it completely

■ Apply mask sheet over face

■ Remove the sheet in 10-20 minutes and gently massage the serum residue into skin until absorbed